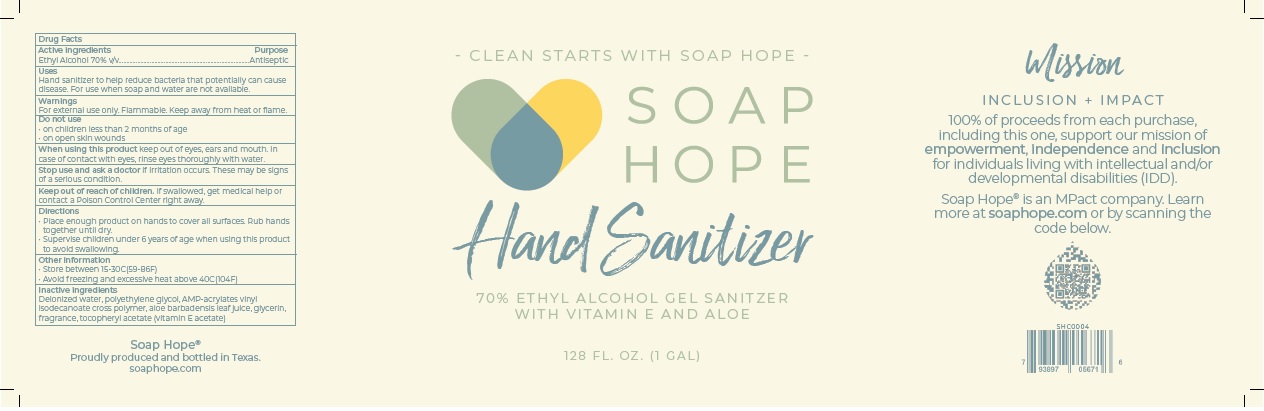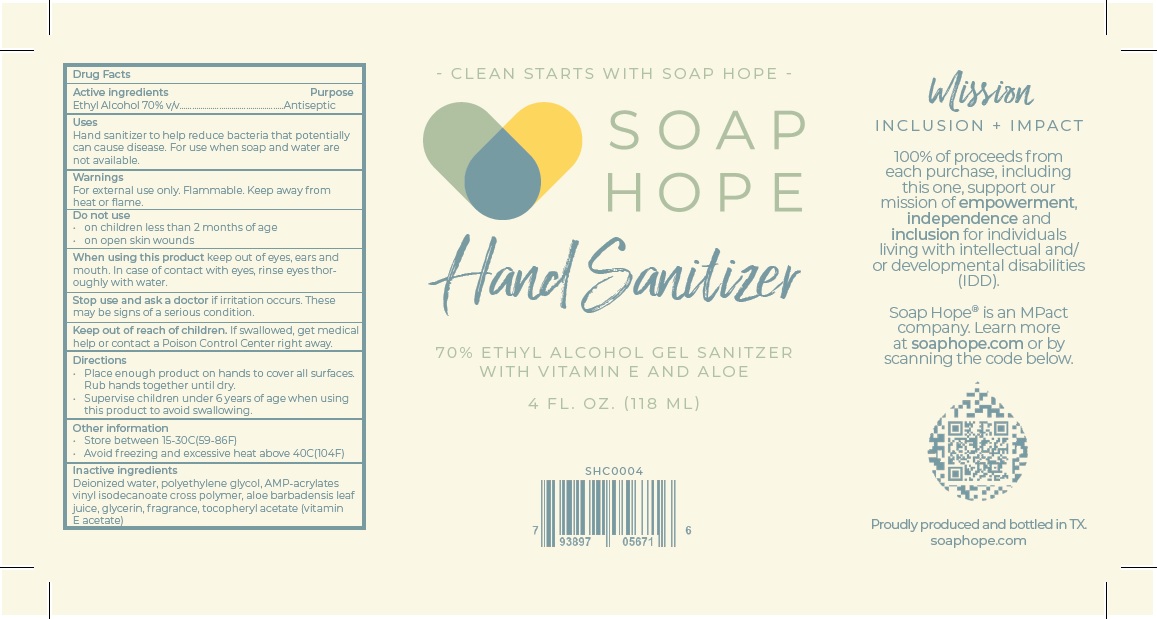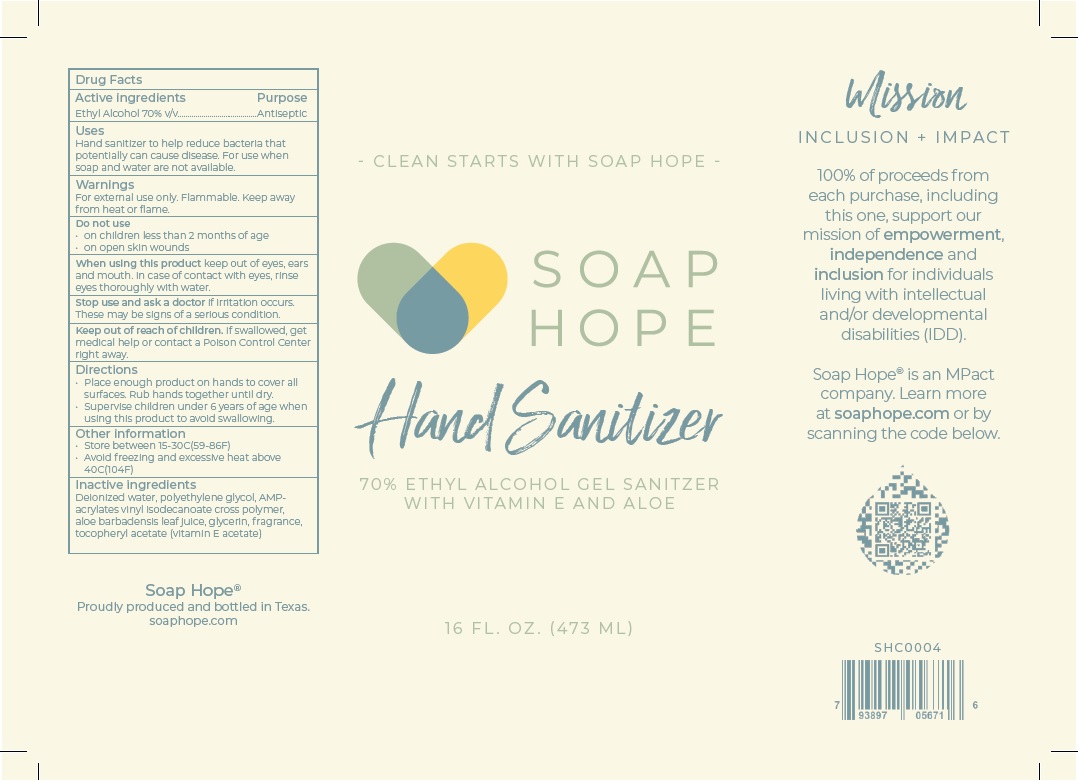 DRUG LABEL: SHCHS001
NDC: 79088-101 | Form: GEL
Manufacturer: Soap Hope
Category: otc | Type: HUMAN OTC DRUG LABEL
Date: 20200711

ACTIVE INGREDIENTS: ALCOHOL 70 mL/100 mL
INACTIVE INGREDIENTS: WATER; POLYETHYLENE GLYCOL, UNSPECIFIED; AMINOMETHYLPROPANOL; ACRYLATES/VINYL ISODECANOATE CROSSPOLYMER (10000 MPA.S NEUTRALIZED AT 0.5%); ALOE VERA LEAF; GLYCERIN; .ALPHA.-TOCOPHEROL ACETATE

SOAP HOPE Hand Sanitizer

Active ingredients

Ethyl Alcohol 70% v/v

Purpose

Antiseptic

Uses

Hand sanitizer to help reduce bacteria that potentially can cause disease. For use when soap and water are not available.

Warnings

For external use only. Flammable. Keep away from heat or flame.

Do not use

• on children less than 2 months of age

• on open skin wounds

When using this product keep out of eyes, ears and mouth. In case of contact with eyes, rinse eyes thoroughly with water.

Stop use and ask a doctor if irritation occurs. These may be signs of a serious condition.

Keep out of reach of children. If swallowed, get medical help or contact a Poison Control Center right away.

Directions

• Place enough product on hands to cover all surfaces. Rub hands together until dry.

• Supervise children under 6 years of age when using this product to avoid swallowing.

Other information

• Store between 15-30C(59-86F)

• Avoid freezing and excessive heat above 40C(104F)

Inactive ingredients

Deionized water, polyethylene glycol, AMP-acrylates vinyl isodecanoate cross polymer, aloe barbadensis leaf juice, glycerin, fragrance, tocopheryl acetate (vitamin E acetate)

- CLEAN STARTS WITH SOAP HOPE -

70% ETHYL ALCOHOL GEL SANITZER WITH VITAMIN E AND ALOE

Mission

INCLUSION + IMPACT

100% of proceeds from each purchase, including this one, support our mission of empowerment, independence and inclusion for individuals living with intellectual and/or developmental disabilities (IDD).

Soap Hope® is an MPact company. Learn more at soaphope.com or by scanning the code below.

Proudly produced and bottled in TX.

soaphope.com